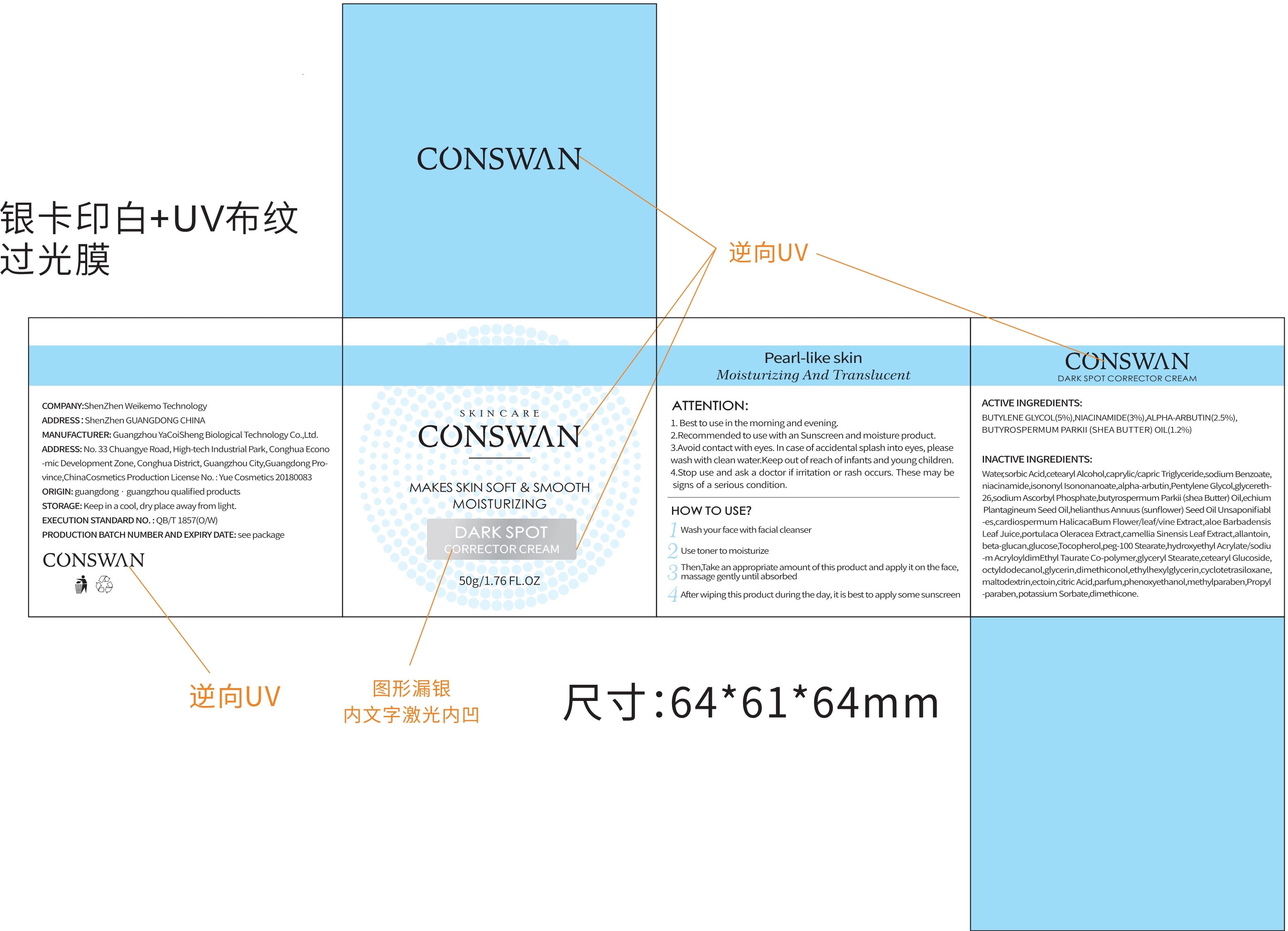 DRUG LABEL: Dark spot corrector
NDC: 81940-001 | Form: CREAM
Manufacturer: Shenzhen  Weikemo  Intelligent Technology CO.,LTD
Category: otc | Type: HUMAN OTC DRUG LABEL
Date: 20210525

ACTIVE INGREDIENTS: NIACINAMIDE 3 g/100 g; ALPHA-ARBUTIN 2.5 g/100 g; BUTYLENE GLYCOL 5 g/100 g; SHEA BUTTER 1.2 g/100 g
INACTIVE INGREDIENTS: ETHYLHEXYLGLYCERIN; PENTYLENE GLYCOL; ISONONYL ISONONANOATE; ISOHEXADECANE; WATER; POLYOXYL 100 STEARATE; CARDIOSPERMUM HALICACABUM FLOWERING TOP; CITRIC ACID MONOHYDRATE; PROPYLPARABEN; TOCOPHEROL; TRICAPRIN; PHENOXYETHANOL; SODIUM ACRYLOYLDIMETHYLTAURATE; GREEN TEA LEAF; GLYCERIN; GLYCERETH-26; CYCLOMETHICONE 4; CETOSTEARYL ALCOHOL; CETEARYL GLUCOSIDE; TEPRALOXYDIM; CURDLAN; SODIUM BENZOATE; ECHIUM PLANTAGINEUM SEED OIL; GLYCERYL MONOSTEARATE; DIMETHICONE; DIMETHICONOL (100000 CST); POLYSORBATE 80; PURSLANE; BUTYROSPERMUM PARKII (SHEA) BUTTER UNSAPONIFIABLES; ANHYDROUS DEXTROSE; METHYLPARABEN; SUNFLOWER OIL; OCTYLDODECANOL; ALOE VERA LEAF; MALTODEXTRIN; ALLANTOIN; SORBIC ACID; POTASSIUM SORBATE; SORBITAN MONOOLEATE; SODIUM ASCORBYL PHOSPHATE 2 g/100 g

81940-001
Dark spot corrector cream

Active Ingredient(s)

BUTYLENE GLYCOL(5%) , NIACINAMIDE(3%) , ALPHA-ARBUTIN(2.5%) , SODIUM ASCORBYL PHOSPHATE(2%) , BUTYROSPERMUM PARKII(SHEA BUTTER) OIL(1.2%)

Purpose

Dark spot corrector

Use

Use toner to moisturize

Then, Take an appropriate amount of this product and apply it on the face, massage gently until absorbed

Warnings

1.Best to use in the morning and evening.
2.Recommended to use with an Sunscreen and moisture product.

Do not use

/

HOW TO USE?

1. Wash your face with facial cleanser
2. Use toner to moisturize
3. Then, Take an appropriate amount of this product and apply it on the face, massage gently until absorbed
4. After wiping this product during the day, it is best to apply some sunscreen

Stop use andask a doctor if irritation or rash occurs.These maybe signs of a serious condition.

KEEP OUT OF REACH OF CHILDREN

Avoid contact with eyes.In case of accidental splash into eyes, please wash with clean water.Keep out of reach of infants and young children.

Directions（ATTENTION：）

1.Best to use in the morning and evening.
2.Recommended to use with an Sunscreen and moisture product.
3.Avoid contact with eyes.In case of accidental splash into eyes, please wash with clean water.Keep out of reach of infants and young children.
4.Stop use andask a doctor if irritation or rash occurs.These maybe signs of a serious condition.

Other information

/

Inactive ingredients

Water, butylene Glycol, dimethicone, cetearyl Alcohol caprylic/capric Triglyceride, niacinamide, isononyl Isononanoate, alpha-ar butin, Pentylene Glycol, glycereth-26, sodium Ascorbyl Phosphate, butyrospermum Parkii(shea Butter) Oil, echium Plan tagineum Seed Oil, helianthus Annuus(sunflower) Seed OilUnsaponifiabl-es, cardiospermumHalicacaBum Flower/leaf/vine Extract, aloe Barbadensis Leaf Juice, portulaca Oleracea Extract, camellia Sinensis Leaf Extract, allantoin, beta-glucan, glucose, Tocopherolpeg-100 Stearate, hydroxyethyl Acrylate/sodiu-m AcryloyldimEthyl Taurate Co-polymer, glyceryl Stearate, cetearyl Glucoside, octyldodecanol, glycerin, dimethiconol, ethylhexyl glycerin, cyclotetra siloxane, maltodextrin, ectoin, citric Acid, parfum, phenoxy ethano, methylparaben, Propyl-paraben, sodium Benzoate, potassium Sorbate, sorbic Acid.

Package Label - Principal Display Panel

81940-001-01 50g